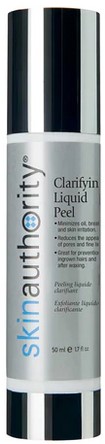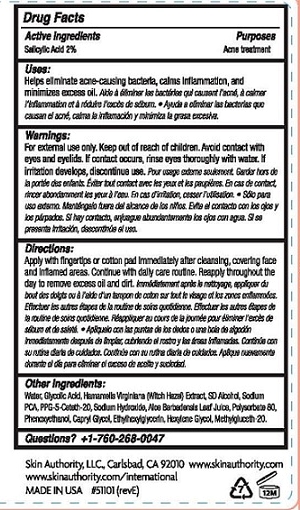 DRUG LABEL: CLARIFYING PEEL
NDC: 46007-102 | Form: GEL
Manufacturer: Skin Authority LLC
Category: otc | Type: HUMAN OTC DRUG LABEL
Date: 20251218

ACTIVE INGREDIENTS: SALICYLIC ACID 2 g/100 mL
INACTIVE INGREDIENTS: WATER; GLYCOLIC ACID; HAMAMELIS VIRGINIANA TOP; ALCOHOL; SODIUM PYRROLIDONE CARBOXYLATE; PPG-5-CETETH-20; SODIUM HYDROXIDE; ALOE VERA LEAF; POLYSORBATE 80; PHENOXYETHANOL; CAPRYLYL GLYCOL; ETHYLHEXYLGLYCERIN; HEXYLENE GLYCOL; METHYL GLUCETH-20

Skin Authority - CLARIFYING LIQUID PEEL (46007-102)

ACTIVE INGREDIENT

SALICYLIC ACID 2%

PURPOSE

ACNE TREATMENT

USES

HELPS ELIMINATE ACNE-CAUSING BACTERIA, CALMS INFLAMMATION, AND MINIMIZES EXCESS OIL.

WARNINGS

FOR EXTERNAL USE ONLY.

AVOID CONTACT WITH EYES AND EYELIDS. IF CONTACT OCCURS, RINSE EYES THOROUGHLY WITH WATER.

IF IRRITATION DEVELOPS, DISCONTINUE USE.

KEEP OUT OF REACH OF CHILDREN.

DIRECTIONS

APPLY WITH FINGERTIPS OR COTTON PAD IMMEDIATELY AFTER CLEANSING, COVERING FACE AND INFLAMED AREAS. CONTINUE WITH DAILY CARE ROUTINE. REAPPLY THROUGHOUT THE DAY TO REMOVE EXCESS OIL AND DIRT.

OTHER INGREDIENTS

WATER, GLYCOLIC ACID, HAMAMELIS VIRGINIANA (WITCH HAZEL) EXTRACT, SD ALCOHOL, SODIUM PCA, PPG-5-CETETH-20, SODIUM HYDROXIDE, ALOE BARBADENSIS LEAF JUICE, POLYSORBATE 80, PHENOXYETHANOL, CAPRYLYL GLYCOL, ETHYLHEXYLGLYCERIN, HEXYLENE GLYCOL, METHYLGLUCETH-20.

QUESTIONS?

+1-760-268-0047